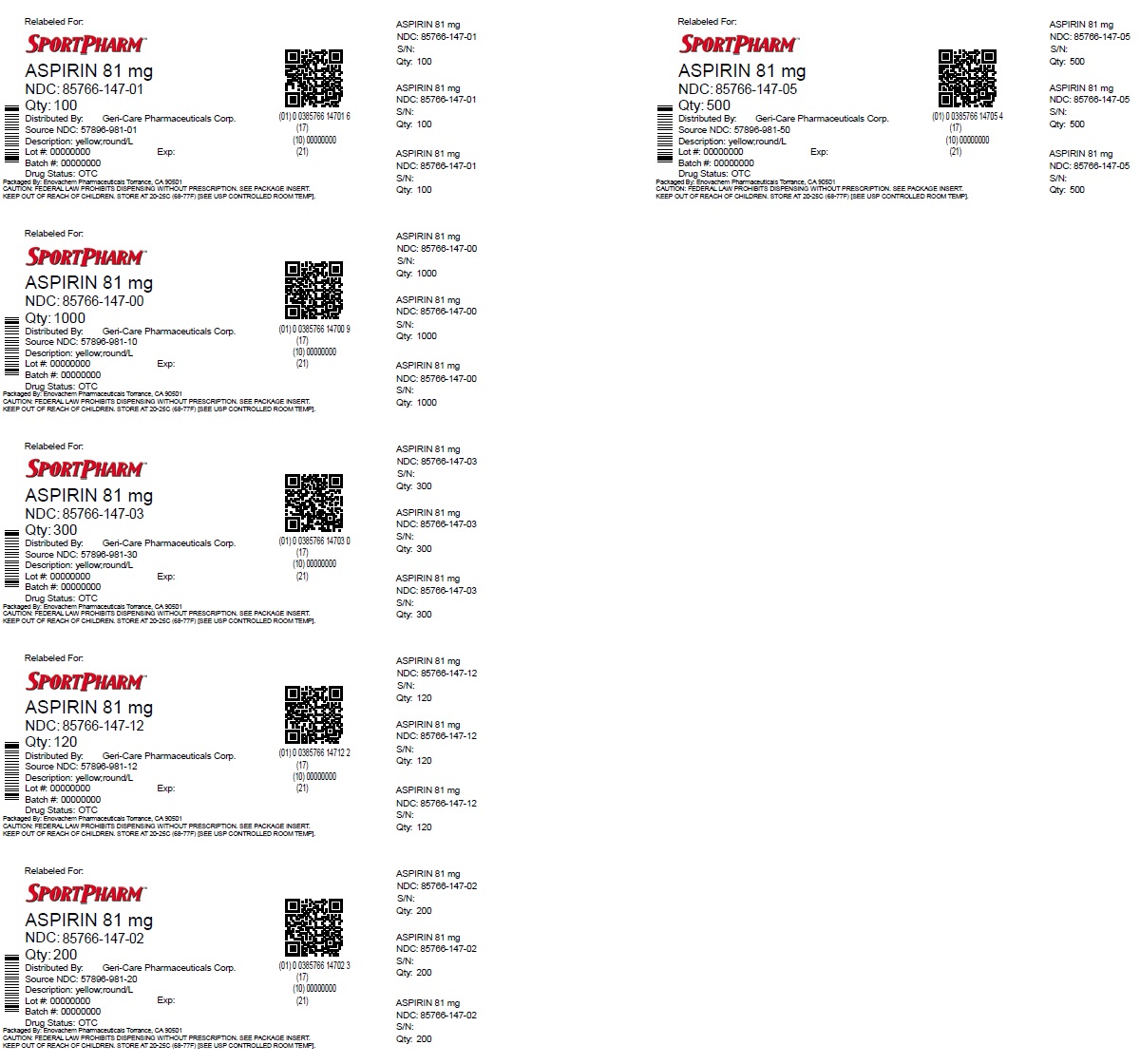 DRUG LABEL: Adult Low Dose Enteric Coated Aspirin
NDC: 85766-147 | Form: TABLET, COATED
Manufacturer: Sportpharm LLC
Category: otc | Type: HUMAN OTC DRUG LABEL
Date: 20260206

ACTIVE INGREDIENTS: ASPIRIN 81 mg/1 1
INACTIVE INGREDIENTS: SHELLAC; SILICON DIOXIDE; DIMETHICONE; SODIUM BICARBONATE; SODIUM LAURYL SULFATE; TALC; TITANIUM DIOXIDE; TRIACETIN; TRIETHYL CITRATE; STARCH, CORN; D&C YELLOW NO. 10; FD&C YELLOW NO. 6; HYPROMELLOSES; METHACRYLIC ACID; CELLULOSE, MICROCRYSTALLINE; POLYDEXTROSE; POLYETHYLENE GLYCOL, UNSPECIFIED

Active ingredient (in each tablet)

Aspirin 81 mg(NSAID)*
*nonsteroidal anti-inflammatory drug

Purpose

Pain reliever

Uses

- for the temporary relief of minor aches and pains
- ask your doctor about other uses for aspirin

Warnings

Reye's Syndrome:Children and teenagers who have or are recovering from chicken pox or flu-like symptoms should not use this product. When using this product, if changes in behavior with nausea and vomiting occur, consult a doctor because these symptoms could be an early sign of Reye's syndrome, a rare but serious illness.

Allergy Alert:Aspirin may cause a severe allergic reaction which may include:

- hives
- facial swelling
- asthma (wheezing)
- shock

Stomach bleeding warning:

This product contains an NSAID, which may cause severe stomach bleeding. The chance is higher if you:

- are age 60 or older
- have had stomach ulcers or bleeding problems
- take a blood thinning (anticoagulant) or steroid drug
- take other drugs containing prescription or nonprescription NSAIDs (aspirin, ibuprofen, naproxen, or others)
- have 3 or more alcoholic drinks every day while using this product
- take more or for a longer time than directed

Do not use

- if your are allergic to aspirin or any other pain reliever/fever reducer.
- if you ever hadan allergic reaction to this product or any of its ingredients

Ask a doctor before use if

- the stomach bleeding warning applies to you
- you are taking a diuretic
- you have a history of stomach problems, such as heartburn
- you have: -high blood pressure -heart disease -liver cirrhosis -kidney disease -asthma

Ask a doctor or pharmacist before use if you are

- taking a prescription drug for diabetes, gout or arthritis

Stop use and ask a doctor if

- an allergic reaction occurs. Seek medical help right away
- you experience any of the following signs of stomach bleeding: -feel faint -vomit blood -have bloody or black stools -have stomach pain that does not get better
- pain gets worse or lasts more than 10 days
- redness or swelling is present
- fever gets worse or lasts more than 3 days
- any new symptoms occur
- ringing in the ears or loss of hearing occurs

These can be signs of a serious condition.

If pregnant or breast-feeding,ask a health professional before use. It is especially important not to use aspirin at 20 weeks or later in pregnancy unless definitely directed to do so by a doctor because it may cause problems in the unborn child or complications during delivery

Keep out of reach of children.In case of overdose , get medical help or contact a Poison Control Center right away.

Directions

- do not exceed recommended dose
- drink a full glass of water with each dose
- swallow whole, do not chew or crush
- adults and children 12 years and older:take 4-8 tablets every 4 hours, as needed, not more than 48 tablets in 24 hours, or as directed by a doctor
- children under 12: ask a doctor

Other information

- store at 20-25°C (68-77°F); excursions permitted between 15°C - 30°C (59°F - 86°F)

Inactive ingredients

cellulose,D&C yellow #10, FD&C yellow #6, hypromellose, methacrylic acid, PEG, polydextrose, silica, simethicone, sodium
bicarbonate, sodium lauryl sulfate, starch, talc, titanium dioxide, triacetin, triethyl citrate, wax.

Questions or comments?

1-800-540-3765